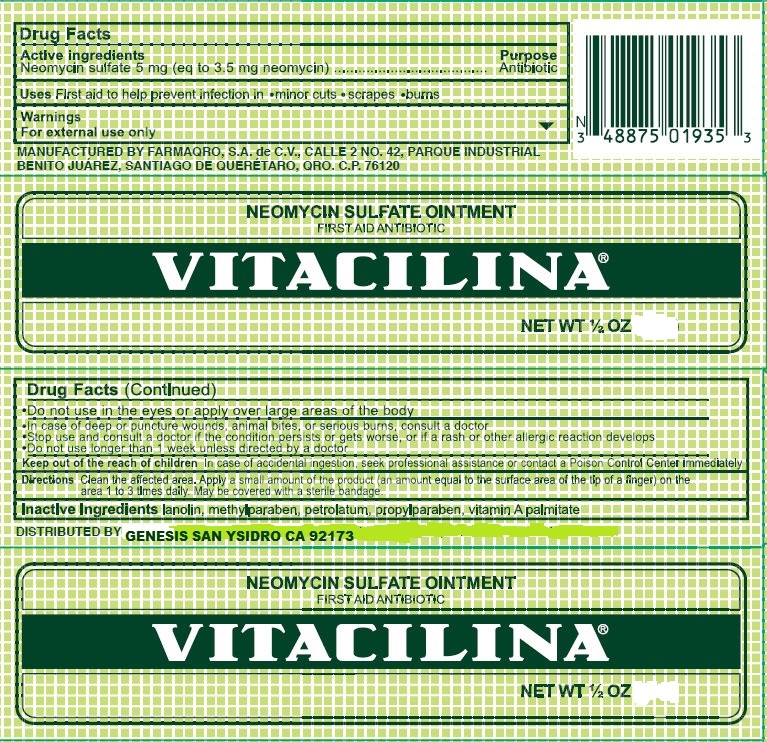 DRUG LABEL: Vitacilina
NDC: 69772-019 | Form: OINTMENT
Manufacturer: Teresa Cecena DBA Genesis
Category: otc | Type: HUMAN OTC DRUG LABEL
Date: 20170203

ACTIVE INGREDIENTS: NEOMYCIN SULFATE 3.5 mg/1 g
INACTIVE INGREDIENTS: LANOLIN; METHYLPARABEN; VITAMIN A PALMITATE; PETROLATUM

ACTIVE INGREDIENT

NEOMYCIN SULFATE 5mg

PURPOSE

Antibootic

USES

Frist aid to help prevent infection in* minor cuts*scrapes*burns

Warnings

For external Use only

DO NOT USE

In the eyes or apply over large areas of the body

Longer that a weel unless directed by doctor

Stop Use

And consult a doctor if the condition persists or gets worse, or if a rash or other allergic reaction develops

KEEP OUT OF REACH OF CHILDREN

In case of accidental ingestion, seek professional assistance or contac a poison control center immediately.

Directions

Clean the affected area. Apply a small amout of the product (an amount equeal to the surface area of the tip of finger) on the area 1 to 3 times daily. May be covered with a sterile bandage.

INDICATIONS AND USAGE

Clean the affected area. Aplly a small amount of the product on the area 1 to 3 times daily.

May be covered with a sterile bandage

INACTIVE INGREDIENT

Lanolin, Methylparaben, Petrolatum, propylparaben, vitamin A palmitate